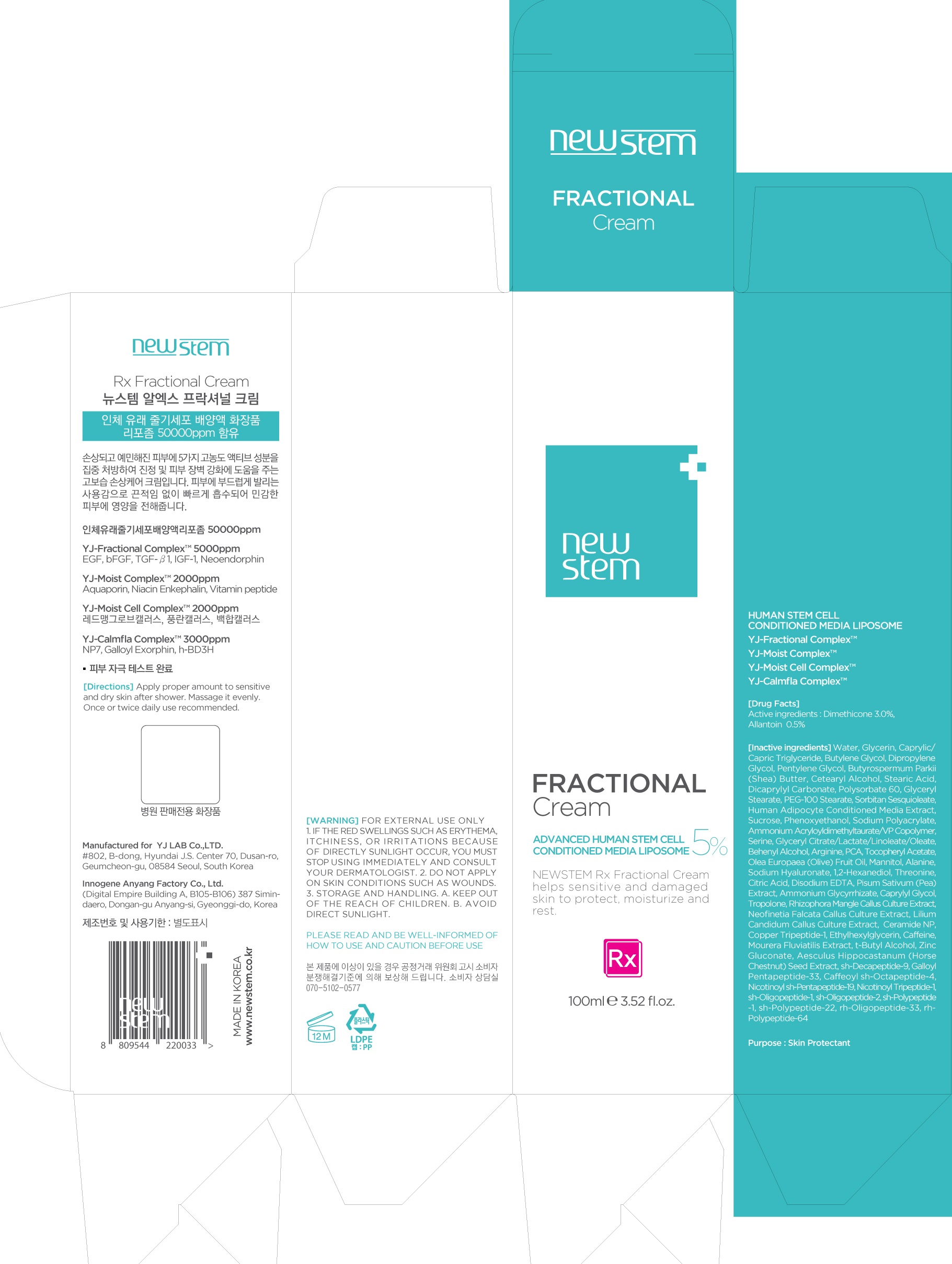 DRUG LABEL: NEWSTEM Rx Fractional
NDC: 71759-030 | Form: CREAM
Manufacturer: Yj Lab Co., Ltd.
Category: otc | Type: HUMAN OTC DRUG LABEL
Date: 20200410

ACTIVE INGREDIENTS: Dimethicone 3.0 g/100 mL; Allantoin 0.5 g/100 mL
INACTIVE INGREDIENTS: Water; Glycerin

ACTIVE INGREDIENT

Active ingredients: Dimethicone 3.0%, Allantoin 0.5%

INACTIVE INGREDIENT

Inactive ingredients: Water, Glycerin, Caprylic/Capric Triglyceride, Butylene Glycol, Dipropylene Glycol, Pentylene Glycol, Butyrospermum Parkii (Shea) Butter, Cetearyl Alcohol, Stearic Acid, Dicaprylyl Carbonate, Polysorbate 60, Glyceryl Stearate, PEG-100 Stearate, Sorbitan Sesquioleate, Human Adipocyte Conditioned Media Extract, Sucrose, Phenoxyethanol, Sodium Polyacrylate, Ammonium Acryloyldimethyltaurate/VP Copolymer, Serine, Glyceryl Citrate/Lactate/Linoleate/Oleate, Behenyl Alcohol, Arginine, PCA, Tocopheryl Acetate, Olea Europaea (Olive) Fruit Oil, Mannitol, Alanine, Sodium Hyaluronate, 1,2-Hexanediol, Threonine, Citric Acid, Disodium EDTA, Pisum Sativum (Pea) Extract, Ammonium Glycyrrhizate, Caprylyl Glycol, Tropolone, Rhizophora Mangle Callus Culture Extract, Neofinetia Falcata Callus Culture Extract, Lilium Candidum Callus Culture Extract, Ceramide NP, Copper Tripeptide-1, Ethylhexylglycerin, Caffeine, Mourera Fluviatilis Extract, t-Butyl Alcohol, Zinc Gluconate, Aesculus Hippocastanum (Horse Chestnut) Seed Extract, sh-Decapeptide-9, Galloyl Pentapeptide-33, Caffeoyl sh-Octapeptide-4, Nicotinoyl sh-Pentapeptide-19, Nicotinoyl Tripeptide-1, sh-Oligopeptide-1, sh-Oligopeptide-2, sh-Polypeptide-1, sh-Polypeptide-22, rh-Oligopeptide-33, rh-Polypeptide-64

PURPOSE

Purpose: Skin Protectant

WARNINGS

Warnings: For external use only 1. If the Red swellings such as erythema, itchiness, or irritations because of directly sunlight occur, you must stop using immediately and Consult your dermatologist. 2. Do not apply on skin conditions such as wounds. 3. Storage and Handling. a. Keep out of the reach of children. b. Avoid direct sunlight.

KEEP OUT OF REACH OF CHILDREN

Uses

Uses: NEWSTEM Rx Fractional Cream helps sensitive and damaged skin to protect, moisturize and rest.

Directions

Directions: Apply proper amount to sensitive and dry skin after shower. Massage it evenly. Once or twice daily use recommended.